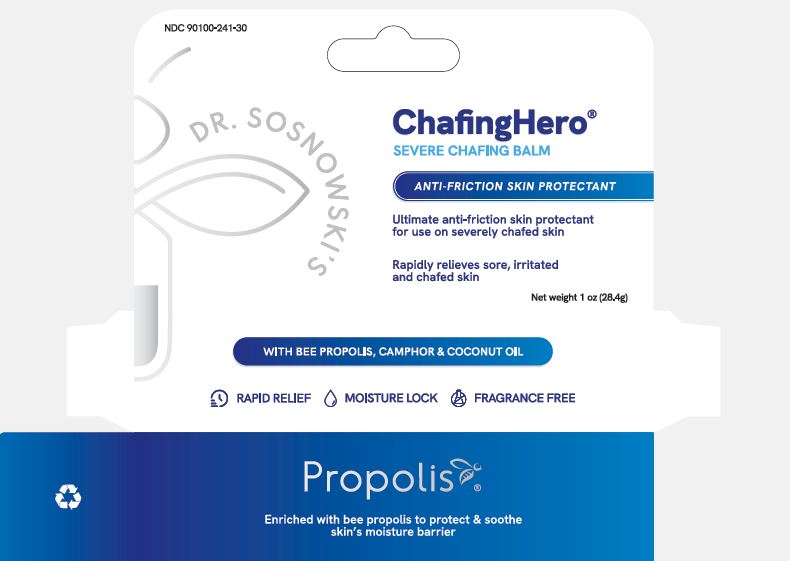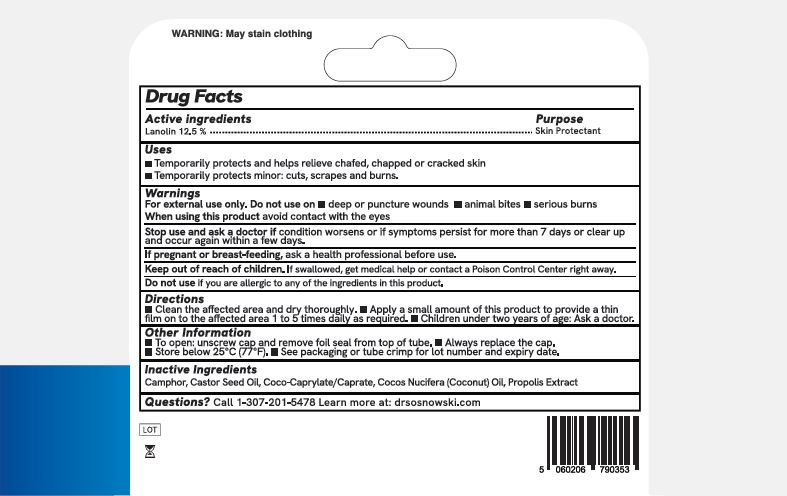 DRUG LABEL: Dr Sosnowskis Chafing Hero
NDC: 90100-241 | Form: STICK
Manufacturer: Herstat (USA) Inc.
Category: otc | Type: HUMAN OTC DRUG LABEL
Date: 20250627

ACTIVE INGREDIENTS: LANOLIN 125 mg/1 g
INACTIVE INGREDIENTS: PROPOLIS WAX; CAMPHOR (NATURAL); RICINUS COMMUNIS (CASTOR) SEED OIL; COCO-CAPRYLATE/CAPRATE; COCOS NUCIFERA (COCONUT) OIL

Dr Snosnowskis Severe Chafing Balm

Drug Facts

Active Ingredient:

Lanolin 12.5%

Purpose:

Skin Protectant

Uses:

- Temporarily protects and helps relieve chafed, chapped or cracked skin
- Temporarily protects minor: cuts, scrapes and burns.

Warnings

For external use only. Do not use on ■ deep or puncture wounds ■ animal bites ■ serious burns

When using this product avoid contact with the eyes

Stop use and ask a doctor if condition worsens or if symptoms persist for more than 7 days or clear up

and occur again within a few days.

PREGNANCY OR BREAST FEEDING

If pregnant or breast-feeding, ask a health professional before use.

Keep out of reach of children. If swallowed, get medical help or contact a Poison Control Center right away.

Do not use if you are allergic to any of the ingredients in this product.

Directions

■ Clean the affected area and dry thoroughly. ■ Apply a small amount of this product to provide a thin
film on to the affected area 1 to 5 times daily as required. ■ Children under two years of age: Ask a doctor.

Other Information

■ To open: unscrew cap and remove foil seal from top of tube. ■ Always replace the cap.
■ Store below 25°C (7 °F). ■ See packaging or tube crimp for lot number and expiry date.

Inactive Ingredients:

Camphor, Castor Seed Oil, Coco-Caprylate/Caprate, Cocos Nucifera (Coconut) Oil, Propolis Extract

Questions:

Questions? Call 1-307-201-5478 Learn more at: drsosnowski.com